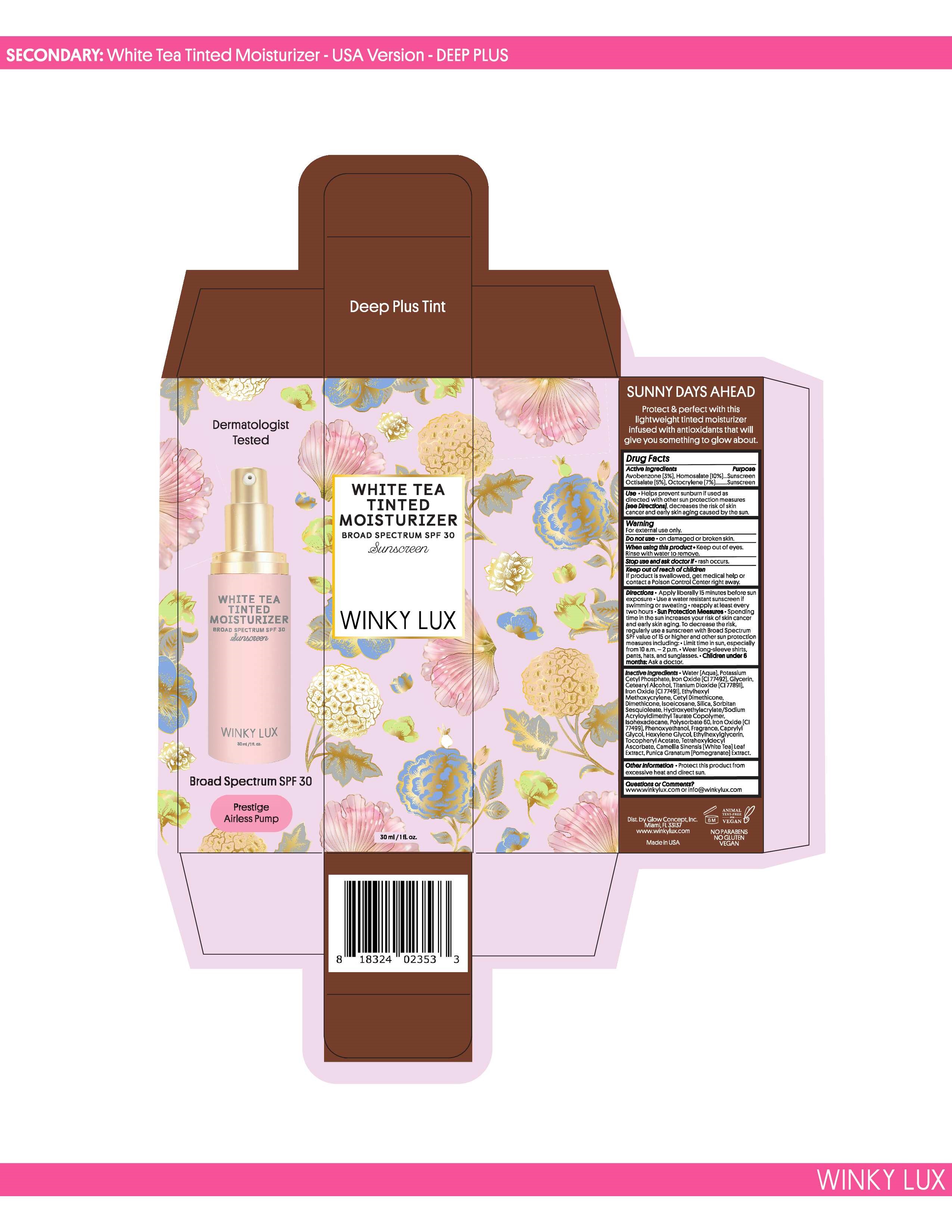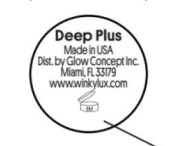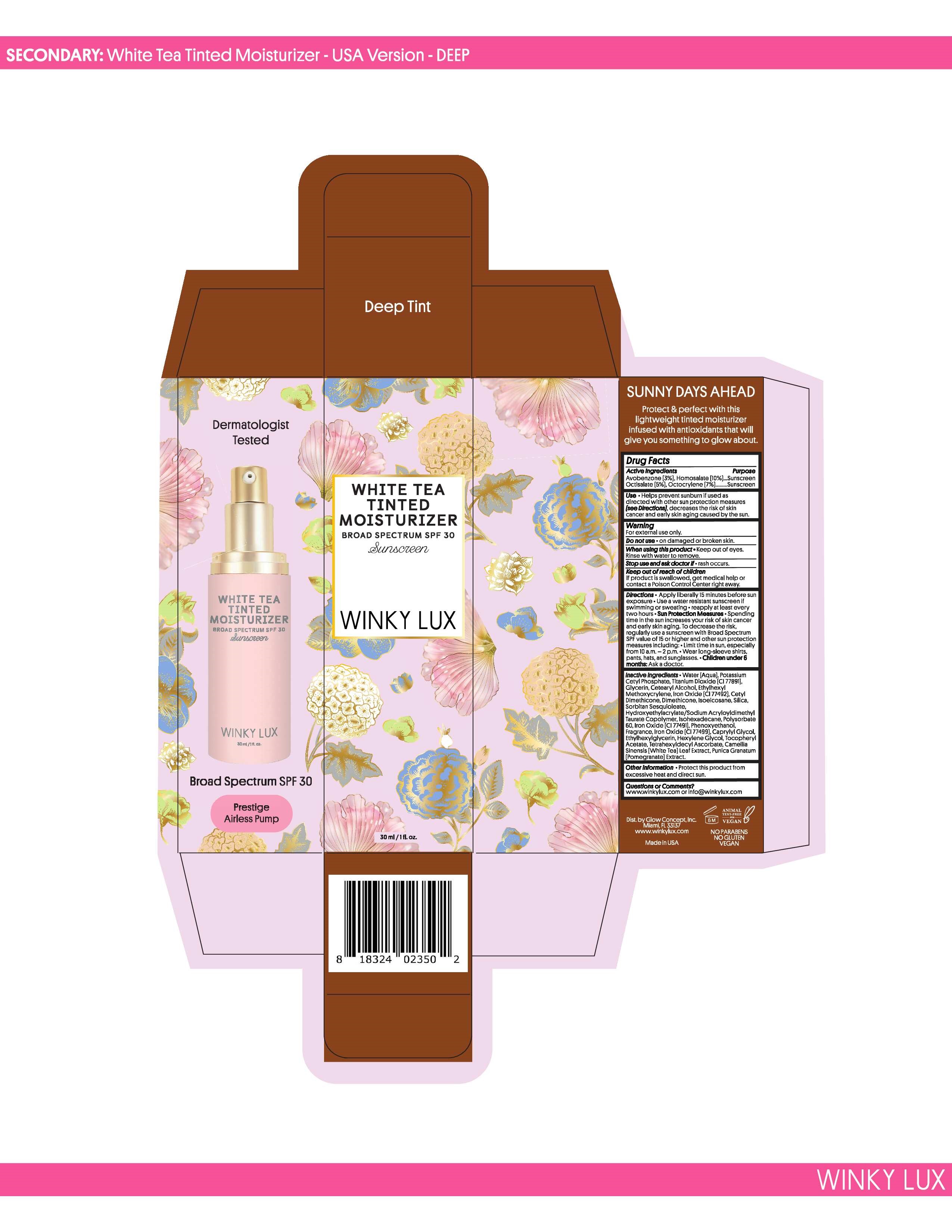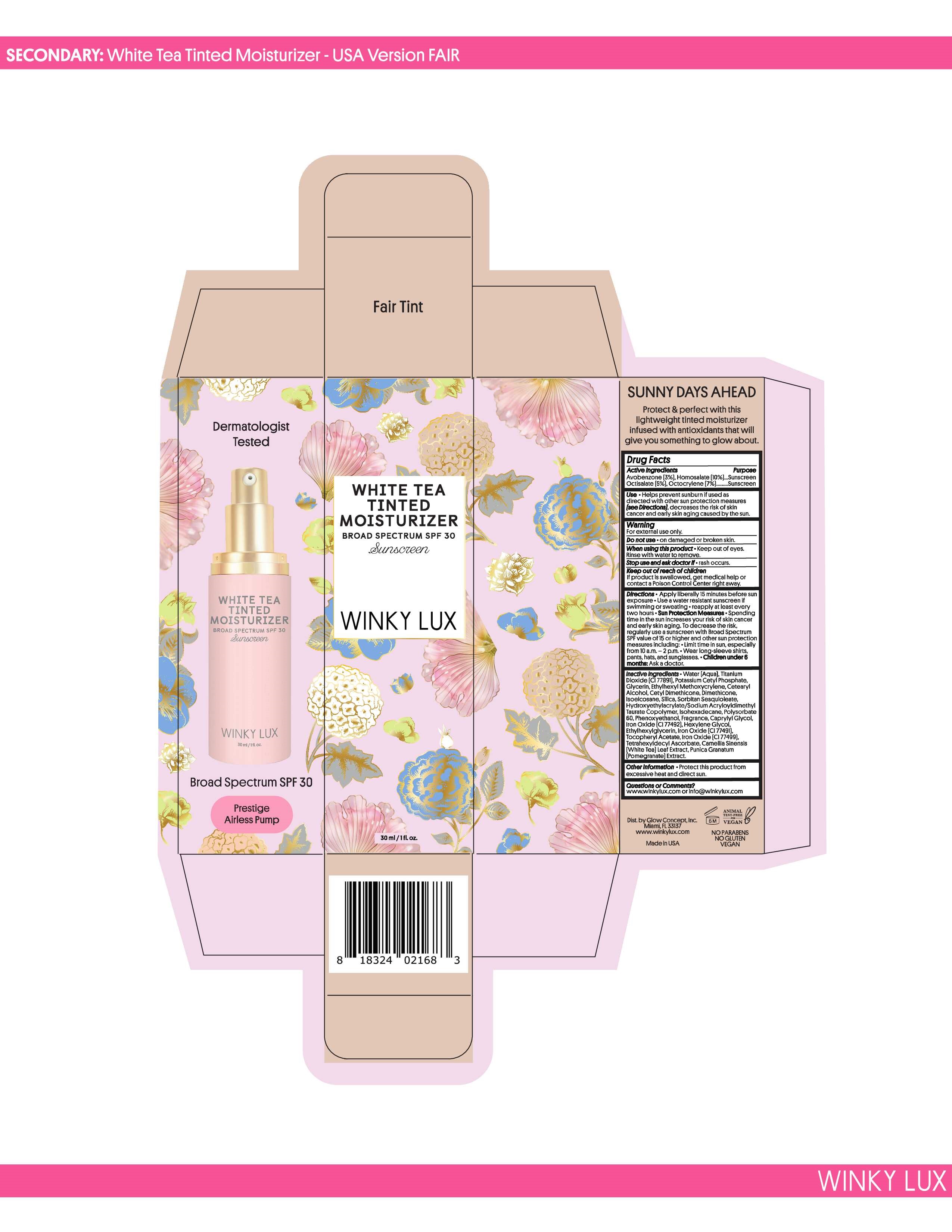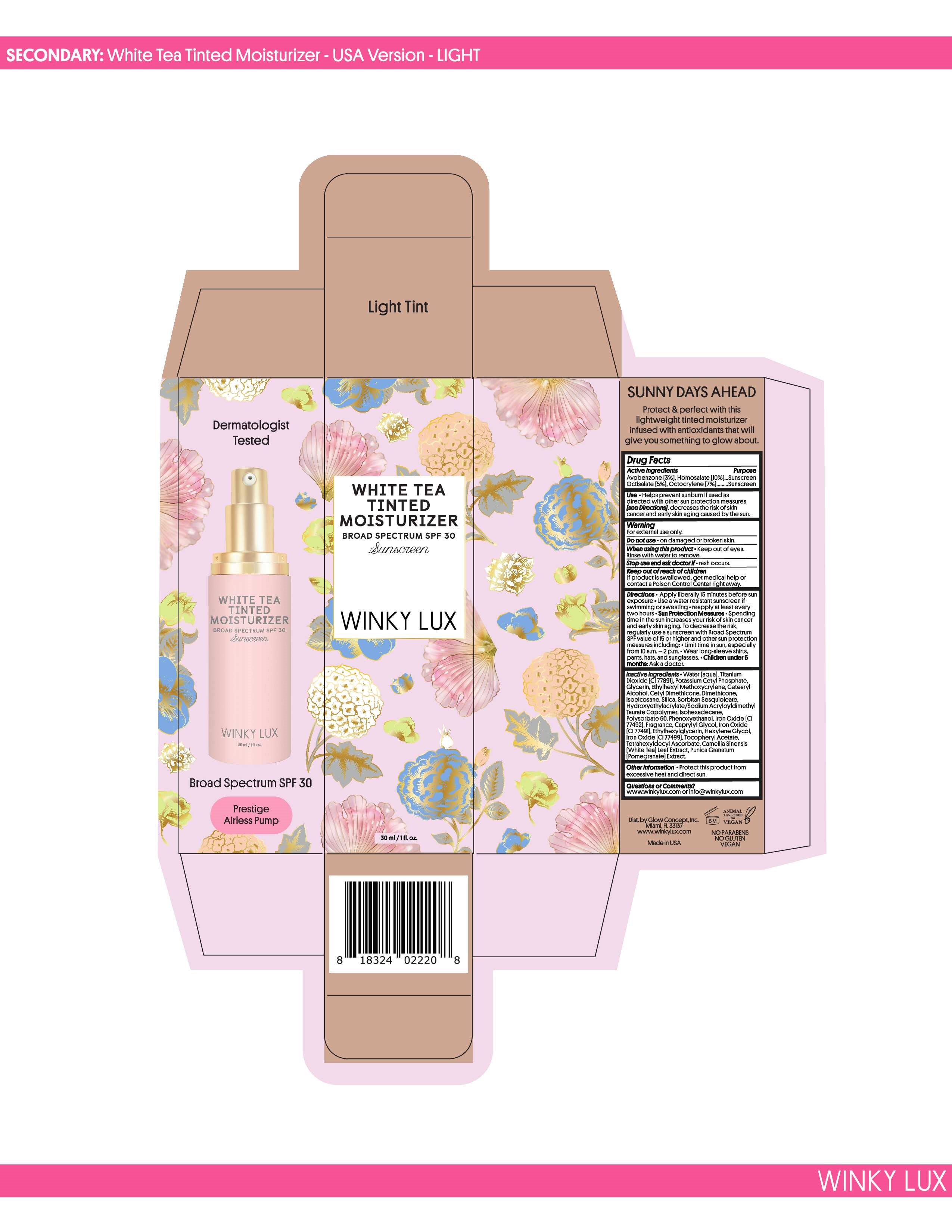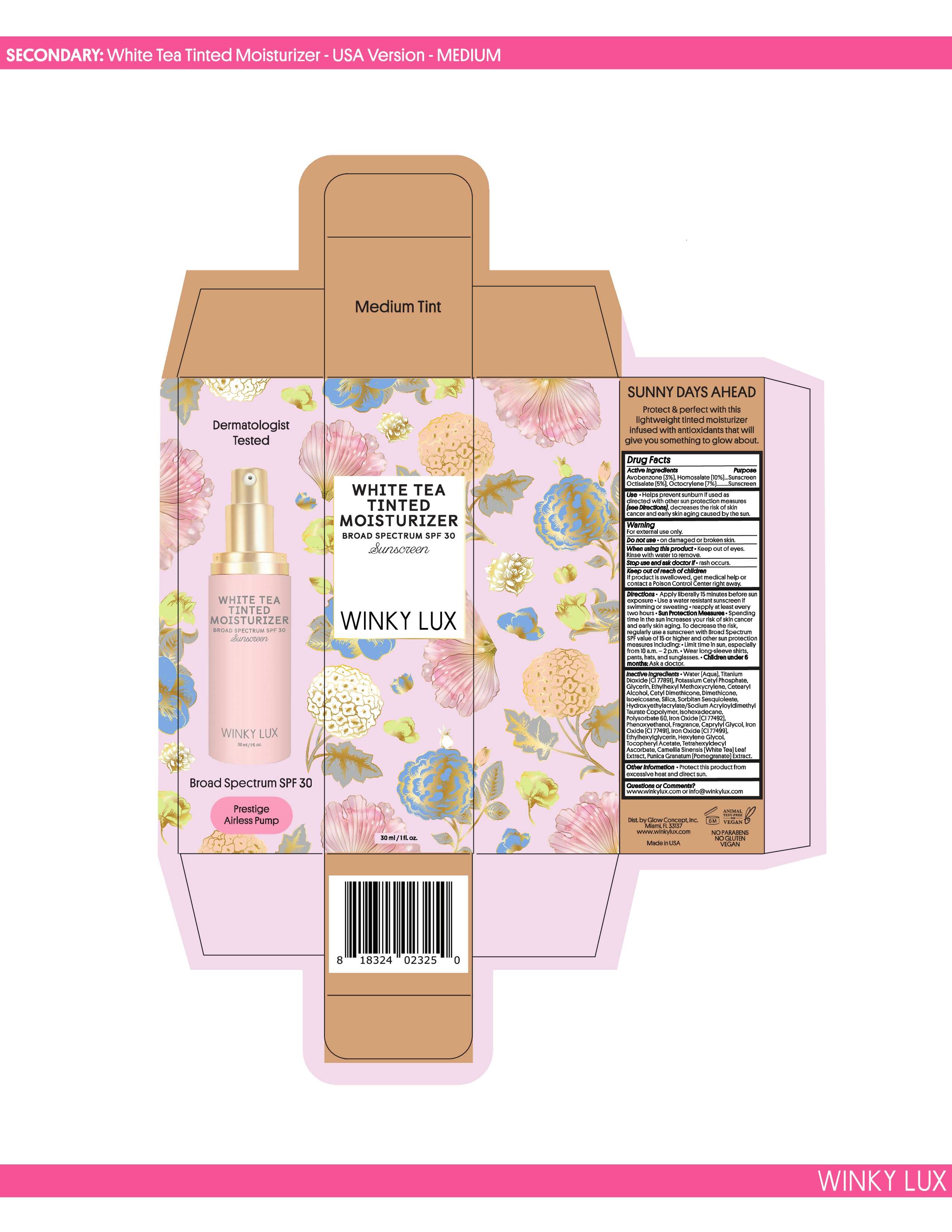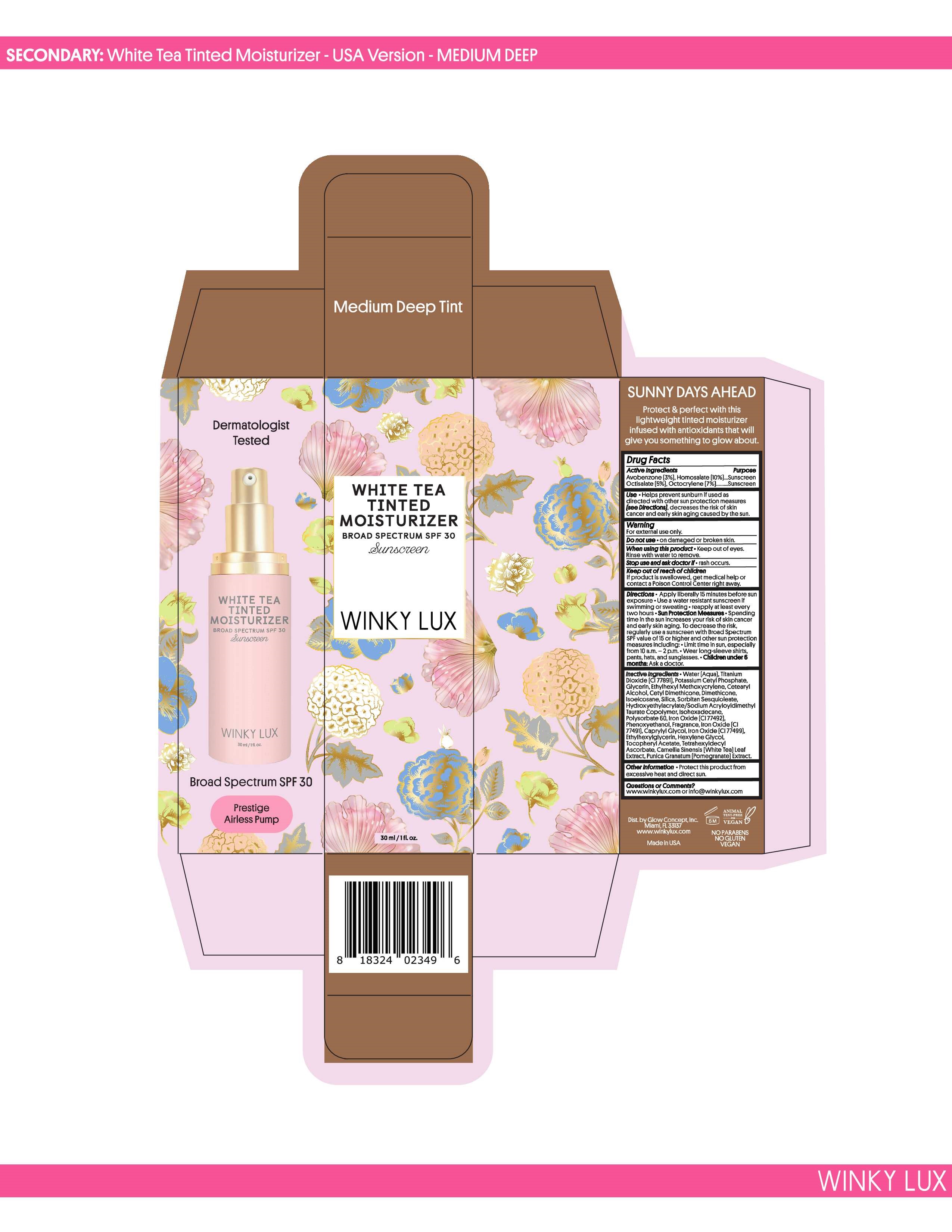 DRUG LABEL: WHITE TEA TINTED MOISTURIZER
NDC: 83022-077 | Form: CREAM
Manufacturer: GLOW CONCEPT INC
Category: otc | Type: HUMAN OTC DRUG LABEL
Date: 20251229

ACTIVE INGREDIENTS: HOMOSALATE 10 mg/1 g; AVOBENZONE 3 mg/1 g; OCTISALATE 5 mg/1 g; OCTOCRYLENE 7 mg/1 g
INACTIVE INGREDIENTS: TITANIUM DIOXIDE; ETHYLHEXYL METHOXYCRYLENE; GLYCERIN; BROWN IRON OXIDE; .ALPHA.-TOCOPHEROL ACETATE; DIMETHICONE; ISOHEXADECANE; POLYSORBATE 60; ETHYLHEXYLGLYCERIN; HEXYLENE GLYCOL; PHENOXYETHANOL; HYDRATED SILICA; SORBITAN SESQUIOLEATE; HYDROXYETHYL ACRYLATE/SODIUM ACRYLOYLDIMETHYL TAURATE COPOLYMER (45000 MPA.S AT 1%); FRAGRANCE 13576; TETRAHEXYLDECYL ASCORBATE; CAMELLIA SINENSIS FLOWER; PUNICA GRANATUM FLOWER; ISOEICOSANE; CAPRYLYL GLYCOL; POTASSIUM CETYL PHOSPHATE

Winky Lux White Tea Tinted Moisturizer Broad Spectrum SPF 30 Sunscreen (30 ml / 1 fl oz)

ACTIVE INGREDIENT

Avobenzone...... 3%

Homosalate....... 10%
Octisalate........... 5%

Octocrylene........ 7%

PURPOSE

SUNSCREEN

WARNINGS

For external use only.

Do not use • on damaged or broken skin.

When using this product • Keep out of eyes.
Rinse with water to remove.

Stop use and ask doctor if • rash occurs.

Keep out of reach of children

If product is swallowed, get medical help or
contact a Poison Control Center right away.

WHEN USING THIS PRODUCT

Keep out of eyes. Rinse with water to remove.

DO NOT USE

On damaged or broken skin

KEEP OUT OF REACH OF CHILDREN

If product is swallowed, get medical help or contact a Poison Control Center right away.

DIRECTIONS

Apply liberally 15 minutes before sun exposure • Use a water resistant sunscreen if swimming or sweating

• reapply at least every two hours

• Sun Protection Measures

• Spending time in the sun increases your risk of skin cancer and early skin aging. To decrease the risk, regularly use a sunscreen with

Broad Spectrum SPF value of 15 or higher and other sun protection measures including:

• Limit time in sun, especially from 10 a.m. – 2 p.m.

• Wear long-sleeve shirts, pants, hats, and sunglasses

OTHER INFORMATION

Protect this product from excessive heat and direct sun.

CHILDREN UNDER 6 MONTHS

Ask a doctor.

INACTIVE INGREDIENT SECTION

Water (Aqua), Titanium Dioxide (CI 77891), Potassium Cetyl Phosphate, Glycerin, Ethylhexyl Methoxycrylene, Cetearyl Alcohol, Cetyl Dimethicone, Dimethicone, Isoeicosane, Silica, Sorbitan Sesquioleate, Hydroxyethylacrylate/Sodium Acryloyldimethyl Taurate Copolymer, Isohexadecane, Polysorbate 60, Phenoxyethanol, Fragrance, Caprylyl Glycol, Iron Oxide (CI 77492), Hexylene Glycol,
Ethylhexylglycerin, Iron Oxide (CI 77491), Tocopheryl Acetate, Iron Oxide (CI 77499), Tetrahexyldecyl Ascorbate, Camellia Sinensis
(White Tea) Leaf Extract, Punica Granatum (Pomegranate) Extract.

QUESTION AND COMMENTS

www.winkylux.com or info@winkylux.com

USE

Helps prevent sunburn if used as directed with other sun protection measures (see Directions), decreases the risk of skin cancer and early skin aging caused by the sun.

WHITE TEA TINTED MOISTURIZER BROAD SPECTRUM SPF 30 SUNSCREEN (PRINCIPAL DISPLAY PANEL)

WHITE TEA TINTED MOISTURIZER

BROAD SPECTRUM SPF 30

SUNSCREEN Fair

Winky Lux

30 mL (1 fl. oz)

PRESTIGE AIRLESS PUMP

Label on bottom of inner packaging

Made in USA

Dist. by Glow Concept Inc.

Miami, FL 33179